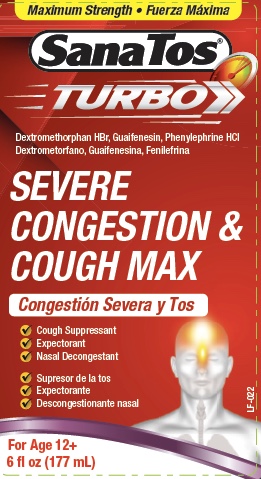 DRUG LABEL: SanaTos Turbo
NDC: 55758-322 | Form: LIQUID
Manufacturer: Pharmadel LLC
Category: otc | Type: HUMAN OTC DRUG LABEL
Date: 20241118

ACTIVE INGREDIENTS: PHENYLEPHRINE HYDROCHLORIDE 10 mg/20 mL; DEXTROMETHORPHAN HYDROBROMIDE 20 mg/20 mL; GUAIFENESIN 400 mg/20 mL
INACTIVE INGREDIENTS: PROPYL GALLATE; FD&C BLUE NO. 1; WATER; ANHYDROUS CITRIC ACID; SORBITOL; GLYCERIN; FD&C RED NO. 40; EDETATE DISODIUM; PROPYLENE GLYCOL; SUCRALOSE; SODIUM BENZOATE; XANTHAN GUM

SanaTos Turbo MS (Apta)

Active ingredients & Purposes

Active ingredient (in each 20 mL) | Purpose
Dextromethorphan HBr 20 mg................... | Cough suppressant
Guaifenesin 400 mg................................... | Expectorant
Phenylephrine HCl 10 mg ………….......… | Nasal decongestant

Uses

- helps loosen phlegm (mucus) and thin bronchial secretions to make coughs more productive
- temporarily relieves common cold/flu symptoms:
- cough due to minor throat and bronchial irritationnasal congestion due to hay fever
- other upper respiratory allergies
- sinus congestion and pressure
- stuffy nose

Warnings

Do not use

- for children under 12 years of age
- if you are now taking a prescription monoamine oxidase inhibitor (MAOI) (certain drugs for depression, psychiatric, or emotional conditions, or Parkinson's disease), or for two weeks after stopping the MAOI drug. If you do not know if your prescription drug contains an MAOI, ask a doctor or pharmacist before taking this product.

Ask a doctor before use if you have

- heart disease
- thyroid disease
- diabetes
- high blood pressure
- a cough that occurs with too much phlegm (mucus)
- a persistent or chronic cough such occurs with smoking, asthma or emphysema
- trouble urinating due to an enlarged prostate gland

When using this product

- do not use more than directed

Stop use and ask a doctor if

- nervousness, dizziness or sleeplessness occur
- a persistent cough or symptoms do not get better within 7 days
- cough comes back, or occurs with a fever, rash or persistent headache. These could be signs of a serious condition.

If pregnant or breast feeding,

ask a health professional before use.

Keep out of reach of children.

In case of overdose, get medical help or contact a Poison Control Center right away.

Directions

- do not exceed recommended dosage
- use dosage cup
- mL = milliliter
- do not take more than 6 doses in any 24-hour period

Age | Dose
adults & children 12 years and older | 20 mL every 4 hours
children under 12 years of age | do not use

Inactive ingredients

anhydrous citric acid, dextrose, D&C red # 33, FD&C red #40, flavors, glycerin, maltitol, propylene glycol, saccharin sodium, sodium benzoate, sucralose, xanthan gum, water

Questions or comments?

+1-866-359-3478 (M-F) 9 AM to 5 PM Eastern or www.pharmadel.com

* This product is not manufactured or distributed by Reckitt Benckiser Inc., distributor of Mucinex® FAST-MAXTM Severe Congestion & Cough